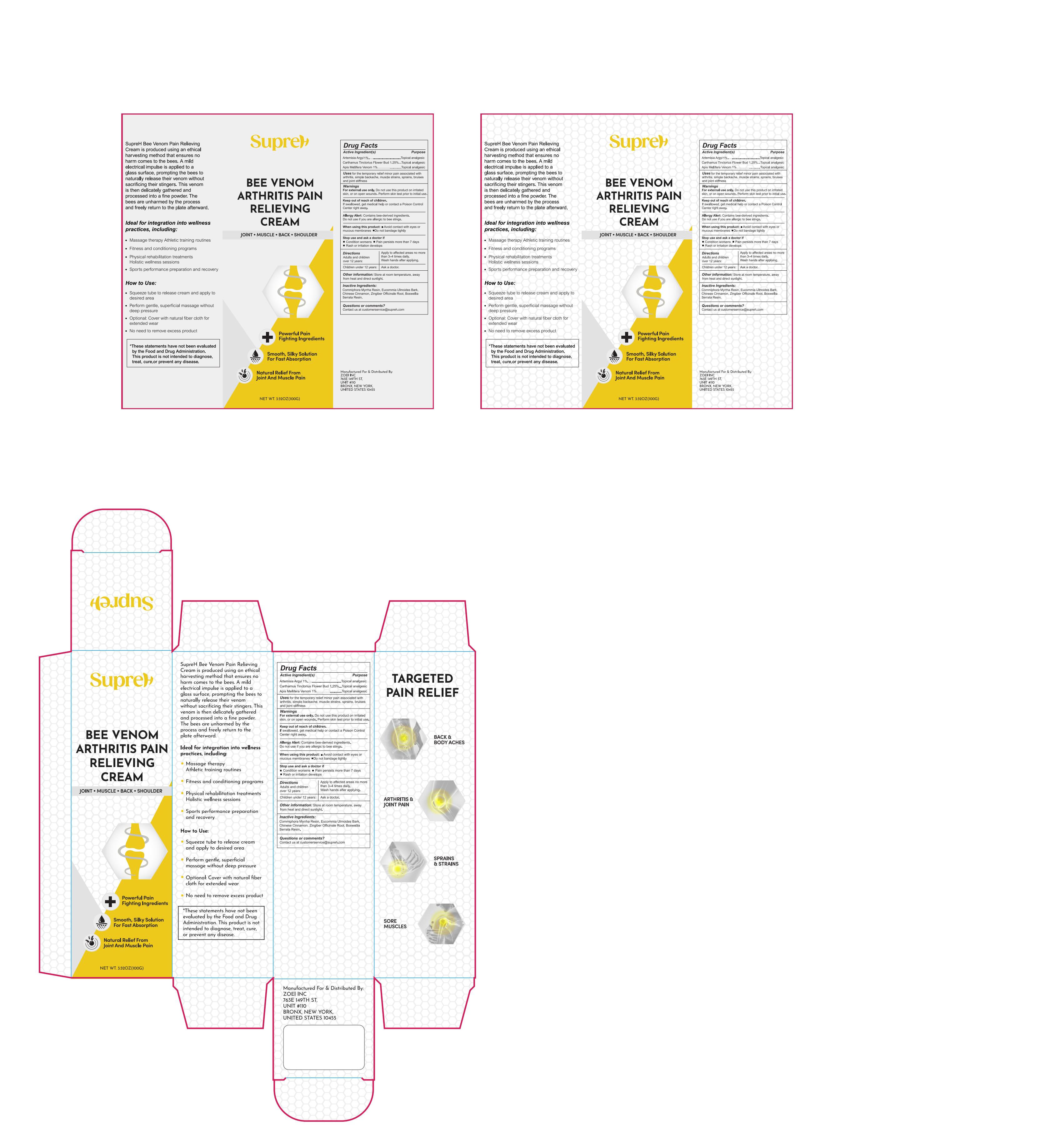 DRUG LABEL: SupreH Bee Venom Arthritis Pain Relieving Cream
NDC: 83818-016 | Form: CREAM
Manufacturer: Shenzhen Xinxin Yunhai Technology Co., Ltd.
Category: otc | Type: HUMAN OTC DRUG LABEL
Date: 20250626

ACTIVE INGREDIENTS: ARTEMISIA ARGYI WHOLE 1 g/100 g; APIS MELLIFERA VENOM 1 g/100 g; CARTHAMUS TINCTORIUS FLOWER BUD 1.25 g/100 g
INACTIVE INGREDIENTS: EUCOMMIA ULMOIDES BARK; BOSWELLIA SERRATA GUM; CHINESE CINNAMON; COMMIPHORA MYRRHA RESIN; GINGER

83818-016

Active Ingredient

Artemisia Argyi, Carthamus Tinctorius Flower Bud, Apis mellifera venom

Purpose

Artemisia Argyi 1%……Topical analgesic
Carthamus Tinctorius Flower Bud 1.25%………Topical analgesic
Apis Mellifera Venom 1%……Topical analgesic

Use

For the temporary relief minor pain associated with arthritis, simple backache, muscle strains, sprains, bruises and joint stiffness

Warnings

For external use only. Do not use this product on irritated skin, or on open wounds. Perform skin test prior to initial use.

Keep Out Of Reach Of Children

If swallowed, get medical help or contact a Poison Control Center right away.

Allergy Alert

Contains bee-derived ingredients. Do not use if you are allergic to bee stings.

When Using this product

Avoid contact with eyes or mucous membranes.
Do not bandage tightly.

Stop use and ask a doctor if

1.Condition worsens
2.Pain persists more than 7 days
3.Rash or irritation develops

Directions

Adult s & children 12 years and over:
Apply to affected areas no more than 3-4 times daily.
Wash hands after applying.

Children under 12 yrs:
Ask a doctor.

Other information

Store at room temperature, away from heat and direct sunlight.

Inactive ingredients

Commiphora Myrrha Resin, Eucommia Ulmoides Bark, Chinese Cinnamon, Zingiber Officinale Root, Boswellia Serrata Resin

Questions or comments?

Contact us at customerservice@supreh.com